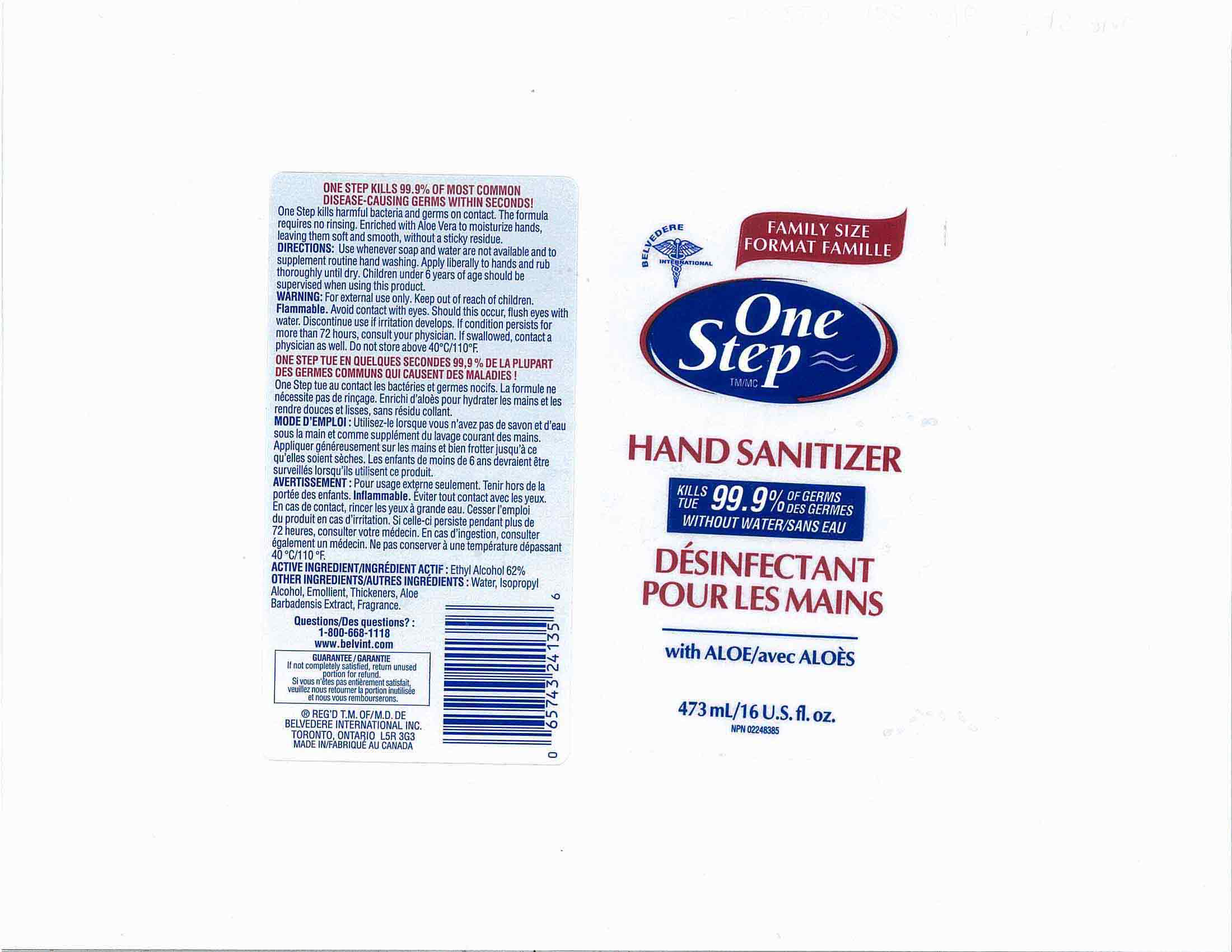 DRUG LABEL: One Step Hand Sanitizer
NDC: 60742-473 | Form: GEL
Manufacturer: Belvedere International Inc.
Category: otc | Type: HUMAN OTC DRUG LABEL
Date: 20120127

ACTIVE INGREDIENTS: ALCOHOL 62 mL/100 mL
INACTIVE INGREDIENTS: WATER; POLYSORBATE 20; ALOE VERA LEAF; CARBOMER 934

DRUG FACTS

ACTIVE INGREDIENT

ETHYL ALCOHOL 62%

PURPOSE

USE WHENEVER SOAP AND WATER ARE NOT AVAILABLE AND TO SUPPLEMENT ROUTINE HAND WASHING APPLY LIBERALLY TO HAND AND RUB THOROUGHLY UNTIL DRY

KEEP OUT OF REACH OF CHILDREN

CHILDREN UNDER 6 YEARS OF AGE SHOULD BE SUPERVISED WHEN USING THIS PRODUCT, KEEP OUT OF REACH OF CHILDREN

INDICATIONS AND USAGE

ONE STEP 473mL

USE WHENEVER SOAP AND WATER ARE NOT AVAILABLE AND TO SUPPLEMENT ROUTINE HAND WASHING APPLY LIBERALLY TO HAND AND RUB THOROUGHLY UNTIL DRY

WARNINGS

FOR EXTERNAL USE ONLY, KEEP OUT OF REACH OF CHILDREN, FLAMMABLE, AVOID CONTACT WITH EYES SHOULD THIS OCCUR FLUSH EYES WITH WATER DISCONTINUE USE IF IRRITATION DEVELOPS IF CONDITION PERSISTS FOR MORE THAN 72 HOURS CONSULT YOUR PHYSICIAN. IF SWALLOWED CONTACT A PHYSICIAN AS WELL. DO NOT STORE ABOVE 40 ^0 C/110 ^0F

DOSAGE AND ADMINISTRATION

USE WHENEVER SOAP AND WATER ARE NOT AVAILABLE AND TO SUPPLEMENT ROUTINE HAND WASHING APPLY LIBERALLY TO HAND AND RUB THOROUGHLY UNTIL DRY

INACTIVE INGREDIENT

WATER, ISOPROPYL ALCOHOL, CARBOMER, ALOE VERA LEAF, POLYSORBATE 20

PACKAGE LABEL

ONE STEP 473mL.jpg